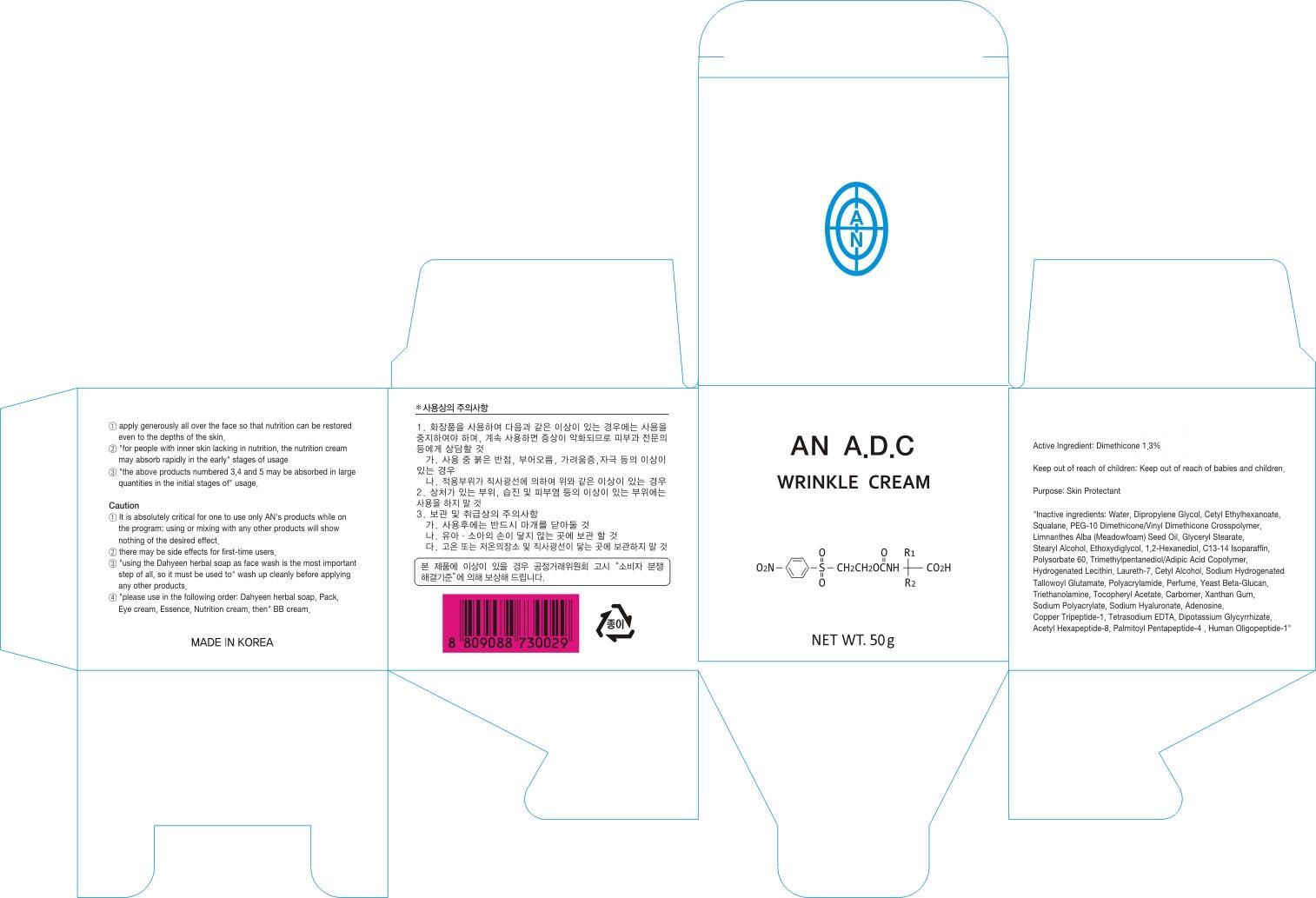 DRUG LABEL: AN ADC WRINKLE
NDC: 69153-050 | Form: CREAM
Manufacturer: AN Co Ltd.
Category: otc | Type: HUMAN OTC DRUG LABEL
Date: 20140929

ACTIVE INGREDIENTS: Dimethicone 0.65 g/50 g
INACTIVE INGREDIENTS: Water; Dipropylene Glycol

ACTIVE INGREDIENT

Active Ingredient: Dimethicone 1.3%

INACTIVE INGREDIENT

Inactive ingredients: Water, Dipropylene Glycol, Cetyl Ethylhexanoate, Squalane, PEG-10 Dimethicone/Vinyl Dimethicone Crosspolymer, Limnanthes Alba (Meadowfoam) Seed Oil, Glyceryl Stearate, Stearyl Alcohol, Ethoxydiglycol, 1,2-Hexanediol, C13-14 Isoparaffin, Polysorbate 60, Trimethylpentanediol/Adipic Acid Copolymer, Hydrogenated Lecithin, Laureth-7, Cetyl Alcohol, Sodium Hydrogenated Tallowoyl Glutamate, Polyacrylamide, Perfume, Yeast Beta-Glucan, Triethanolamine, Tocopheryl Acetate, Carbomer, Xanthan Gum, Sodium Polyacrylate, Sodium Hyaluronate, Adenosine, Copper Tripeptide-1, Tetrasodium EDTA, Dipotassium Glycyrrhizate, Acetyl Hexapeptide-8, Palmitoyl Pentapeptide-4 , Human Oligopeptide-1

PURPOSE

Purpose: Skin Protectant

Caution

1. It is absolutely critical for one to use only AN's products while on the program; using or mixing with any other products will show nothing of the desired effect.
2. There may be side effects for first-time users.
3. Using the Dahyeen herbal soap as face wash is the most important step of all, so it must be used to wash up cleanly before applying any other products.
4. Please use in the following order: Dahyeen herbal soap, Pack, Eye cream, Essence, Nutrition cream, then BB cream.

Keep out of reach of children: Keep out of reach of babies and children.

INDICATIONS & USAGE

1. Apply generously all over the face so that nutrition can be restored even to the depths of the skin.
2. For people with inner skin lacking in nutrition, the nutrition cream may absorb rapidly in the early stages of usage
3. The above products numbered 3,4 and 5 may be absorbed in large quantities in the initial stages of usage.

DOSAGE & ADMINISTRATION

1. Apply generously all over the face so that nutrition can be restored even to the depths of the skin.
2. For people with inner skin lacking in nutrition, the nutrition cream may absorb rapidly in the early stages of usage
3. The above products numbered 3,4 and 5 may be absorbed in large quantities in the initial stages of usage.